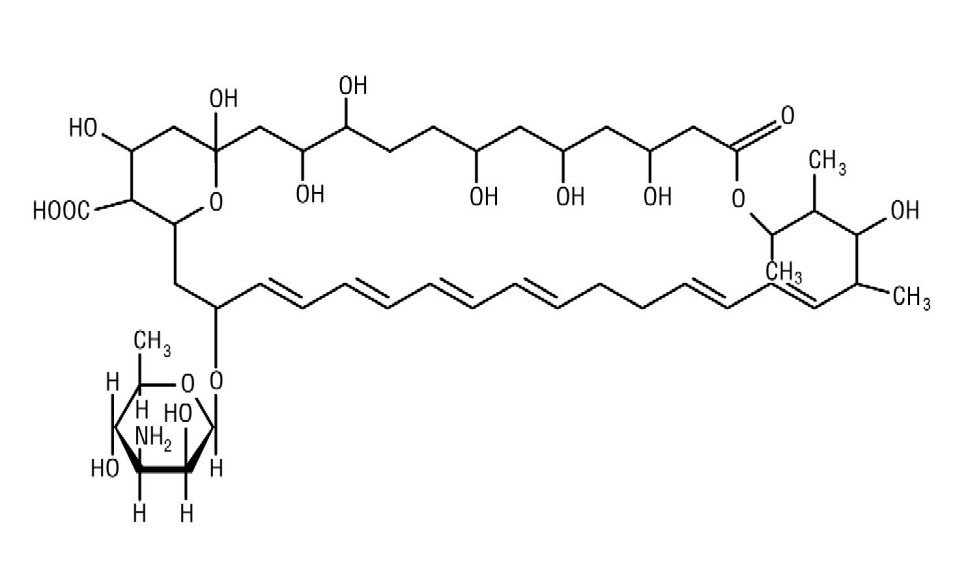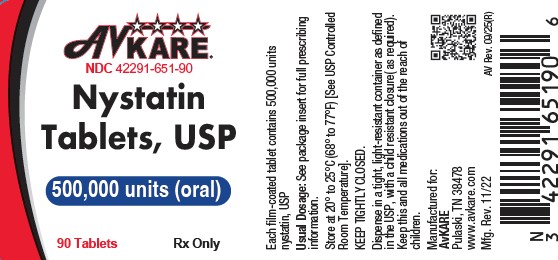 DRUG LABEL: Nystatin
NDC: 42291-651 | Form: TABLET, FILM COATED
Manufacturer: AvKARE
Category: prescription | Type: HUMAN PRESCRIPTION DRUG LABEL
Date: 20250918

ACTIVE INGREDIENTS: NYSTATIN 500000 [USP'U]/1 1
INACTIVE INGREDIENTS: STARCH, CORN; POVIDONE K29/32; CELLULOSE, MICROCRYSTALLINE; SODIUM STARCH GLYCOLATE TYPE A POTATO; TALC; MAGNESIUM STEARATE; WATER; ISOPROPYL ALCOHOL

Nystatin Tablets USP
Rx only

DESCRIPTION

Nystatin, USP is an antimycotic polyene antibiotic obtained from Streptomyces noursei. Its structural formula:

C47H75NO17 M.W. 926.13

Nystatin tablets USP contain the inactive ingredients: Corn Starch, Povidone, Compressible Sugar, Microcrystalline Cellulose, Sodium Starch Glycolate, Talc, Magnesium Stearate, Purified Water, and Coloring.

CLINICAL PHARMACOLOGY

Pharmacokinetics

Gastrointestinal absorption of nystatin is insignificant. Most orally administered nystatin is passed unchanged in the stool. In patients with renal insufficiency receiving oral therapy with conventional dosage forms, significant plasma concentrations of nystatin may occasionally occur.

Microbiology

Nystatin is both fungistatic and fungicidal in vitro against a wide variety of yeasts and yeast like fungi. Candida albicans demonstrates no significant resistance to nystatin in vitro on repeated subculture in increasing levels of nystatin; other Candida species become quite resistant. Generally, resistance does not develop in vivo. Nystatin acts by binding to sterols in the cell membrane of susceptible Candida species with a resultant change in membrane permeability allowing leakage of intracellular components. Nystatin exhibits no appreciable activity against bacteria, protozoa, or viruses.

INDICATIONS AND USAGE

Nystatin tablets are intended for the treatment of non-esophageal mucus membrane gastrointestinal candidiasis.

CONTRAINDICATIONS

Nystatin Tablets are contraindicated in patients with a history of hypersensitivity to any of their components.

PRECAUTIONS

General

This medication is not to be used for the treatment of systemic mycoses. Discontinue treatment if sensitization or irritation is reported during use.

Carcinogenesis, Mutagenesis, Impairment of Fertility

No long-term animal studies have been performed to evaluate carcinogenic potential. There also have been no studies to determine mutagenicity or whether this medication affects fertility in males or females.

Pregnancy

Teratogenic Effects

Pregnancy Category C

Animal reproduction studies have not been conducted with nystatin. It is also not known whether nystatin can cause fetal harm when administered to a pregnant woman or can affect reproduction capacity. Nystatin should be given to a pregnant woman only if clearly needed.

Nursing Mothers

It is not known whether nystatin is excreted in human milk. Because many drugs are excreted in human milk, caution should be exercised when nystatin is administered to a nursing woman.

ADVERSE REACTIONS

Nystatin is well tolerated even with prolonged therapy. Oral irritation and sensitization have been reported (see PRECAUTIONS, General).

Gastrointestinal

Diarrhea (including one case of bloody diarrhea), nausea, vomiting, gastrointestinal upset/disturbances.

Dermatologic

Rash, including urticaria has been reported rarely. Stevens-Johnson syndrome has been reported very rarely.

Other

Tachycardia, bronchospasm, facial swelling, and nonspecific myalgia have also been rarely reported.

To report SUSPECTED ADVERSE REACTIONS contact AvKARE at 1-855-361-3993; email drugsafety@avkare.com; or FDA at 1-800-FDA-1088 or www.fda.gov/medwatch.

OVERDOSAGE

Oral doses of nystatin in excess of five million units daily have caused nausea and gastrointestinal upset. There have been no reports of serious toxic effects of superinfections (see CLINICAL PHARMACOLOGY, Pharmacokinetics).

DOSAGE AND ADMINISTRATION

The usual therapeutic dosage is one to two tablets (500,000 to 1,000,000 units nystatin) three times daily. Treatment should generally be continued for at least 48 hours after clinical cure to prevent relapse.

HOW SUPPLIED

Nystatin Tablets USP, 500,000 Units are round, convex, brown, film-coated tablet debossed with 93 on one side and 983 on the reverse and are packaged in bottles of 90 tablets (NDC 42291-651-90).

Store at 20° and 25°C (68° and 77°F) [See USP Controlled Room Temperature].

Dispense in a tight, light-resistant container as defined in the USP, with a child-resistant closure (as required).

Keep tightly closed.
KEEP THIS AND ALL MEDICATIONS OUT OF THE REACH OF CHILDREN.

Manufactured For:
AvKARE

Pulaski, TN 38478

Mfg. Rev. 11/22

AV Rev. 09/25(M)